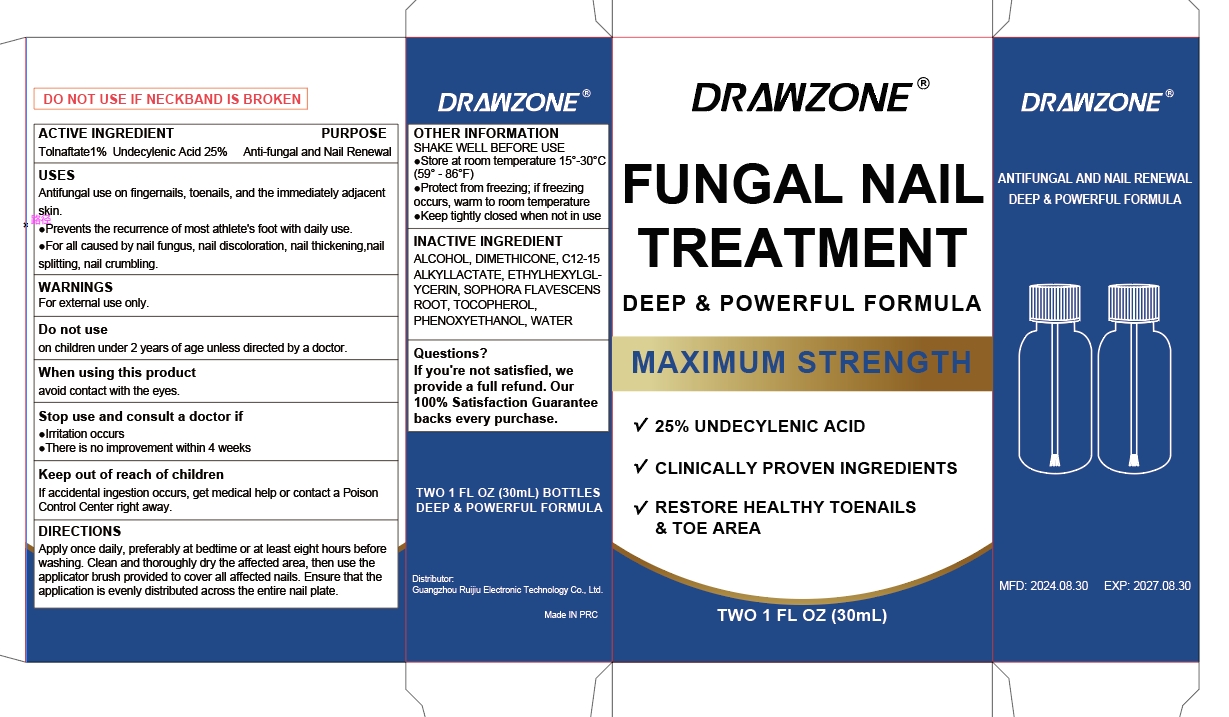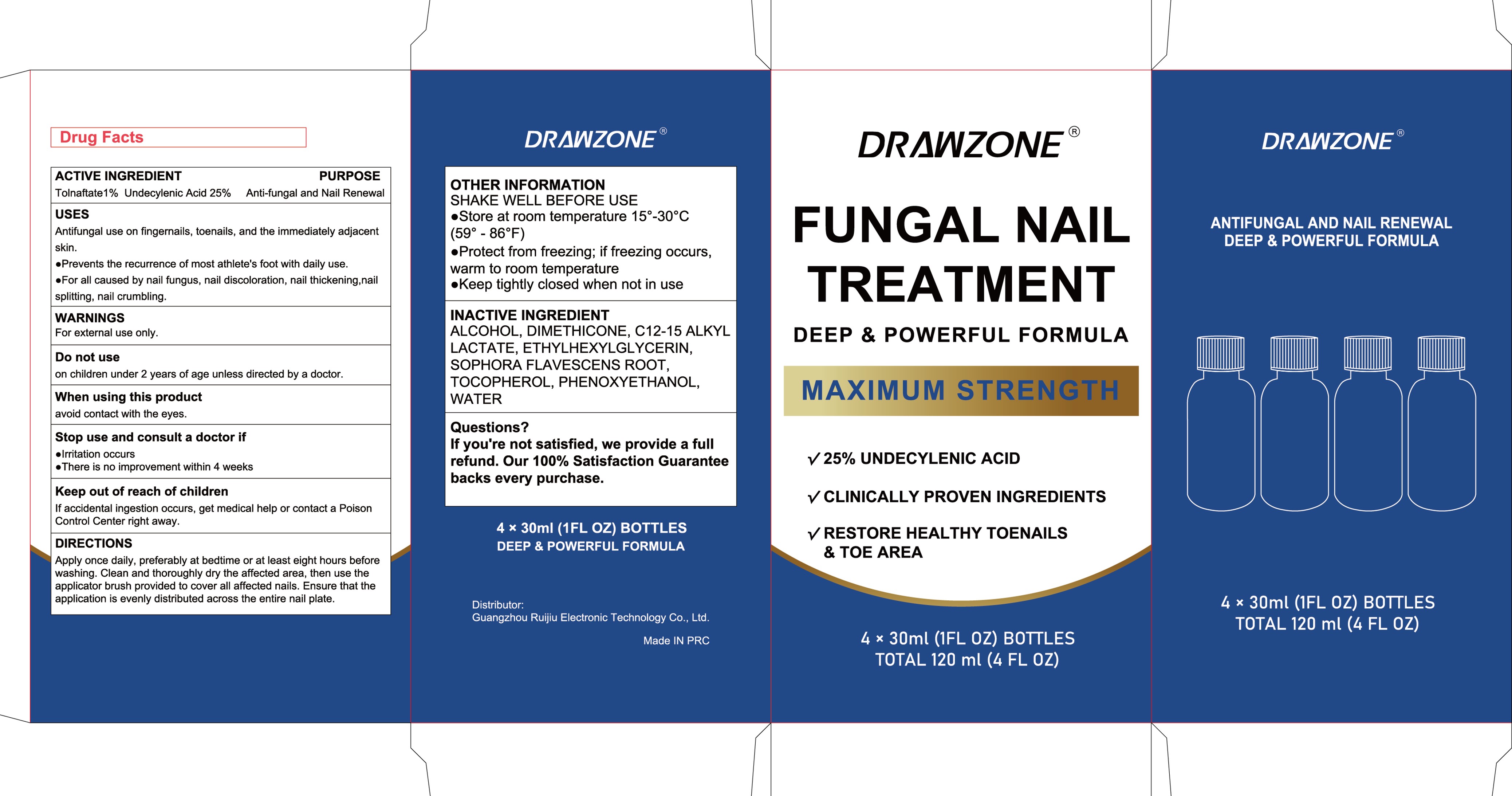 DRUG LABEL: FUNGAL NAIL TREATMENT MAXIMUM STRENGTH Liquid
NDC: 83767-501 | Form: LIQUID
Manufacturer: Guangzhou Ruijiu Electronic Technology Co., Ltd.
Category: otc | Type: HUMAN OTC DRUG LABEL
Date: 20241219

ACTIVE INGREDIENTS: TOLNAFTATE 1 g/100 mL; UNDECYLENIC ACID 25 g/100 mL
INACTIVE INGREDIENTS: C12-15 ALKYL LACTATE; SOPHORA FLAVESCENS ROOT; DIMETHICONE; ETHYLHEXYLGLYCERIN; PHENOXYETHANOL; TOCOPHEROL; ALCOHOL; WATER

FUNGAL NAIL TREATMENT MAXIMUM STRENGTH Liquid

FUNGAL NAIL TREATMENT MAXIMUM STRENGTH Liquid

ACTIVE INGREDIENT

Tolnaftate 1%
Undecylenic Acid 25%

PURPOSE

Anti-fungal and Nail Renewal

INDICATIONS AND USAGE

Antifungal use on fingemails, toenails, and the immediately adjacent skin.
Prevents the recurence of most athlete's foot with daily use
For all caused by nail fungus, nail discoloration, nail thickening,nailsplitting, nail crumbling.

WARNINGS

For external use only.

DO NOT USE

on children under 2 years of age unless directed by a doctor

WHEN USING

avoid contact with the eyes.

STOP USE

Imitation occurs
There is no improvement within 4 weeks

KEEP OUT OF REACH OF CHILDREN

If accidental ingestion occurs, get medical help or contact a PoisonControl Center right away.

DOSAGE AND ADMINISTRATION

Apply once daily, preferably at bedtime or at least eight hours beforewashing. Clean and thoroughly dry the affected area, then use theapplicator brush provided to cover all affected nails. Ensure that theapplication is evenly distrnbuted across the entire nail plate

STORAGE AND HANDLING

Store at room temperature 15--30°C(59°-86°F)
Protect from freezing; if freezingoccurs, wamm to room temperature
Keep tightly closed when not in use

INACTIVE INGREDIENT

ALCOHOL
DIMETHICONE
C12-15 ALKYL LACTATE
ETHYLHEXYLGLYCERIN
SOPHORA FLAVESCENS ROOT
TOCOPHEROL
PHENOXYETHANOL
WATER